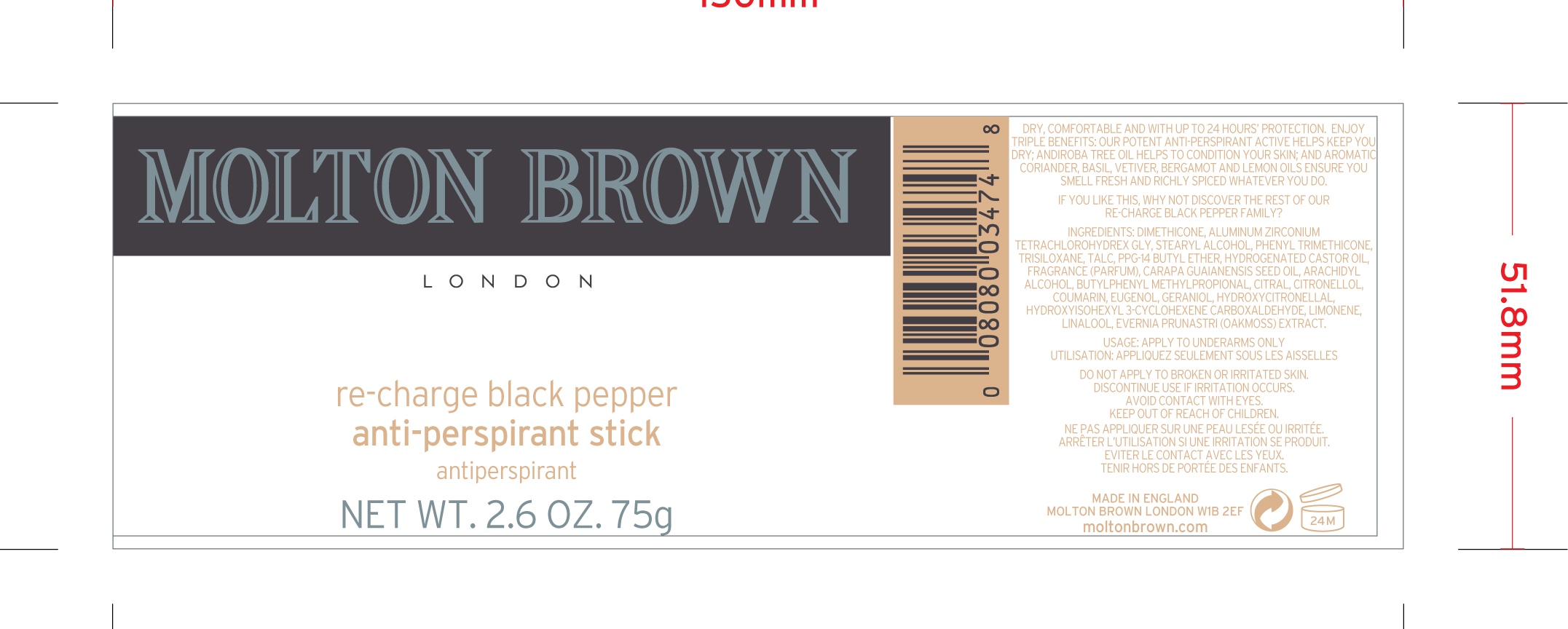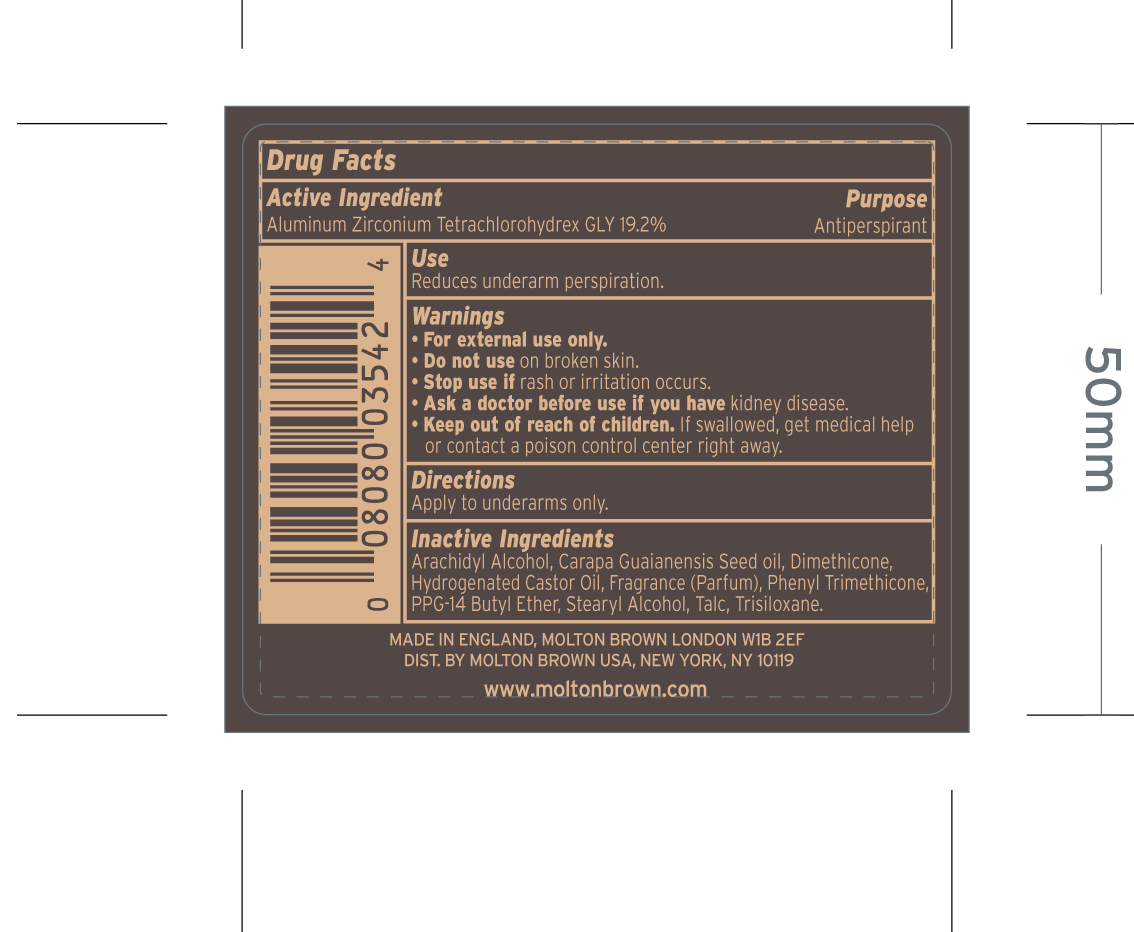 DRUG LABEL: Re-Charge Black Pepper Antiperspirant
NDC: 68814-489 | Form: STICK
Manufacturer: Molton Brown LTD
Category: otc | Type: HUMAN OTC DRUG LABEL
Date: 20160407

ACTIVE INGREDIENTS: ALUMINUM ZIRCONIUM TETRACHLOROHYDREX GLY 19.2 g/100 g
INACTIVE INGREDIENTS: ARACHIDYL ALCOHOL; CARAPA GUIANENSIS SEED OIL; DIMETHICONE; HYDROGENATED CASTOR OIL; PHENYL TRIMETHICONE; PPG-14 BUTYL ETHER; STEARYL ALCOHOL; TALC; TRISILOXANE

Re-charge black pepper anti-perspirant stick

ACTIVE INGREDIENT

Aluminum Zirconium Tetra chlorohydrex GLY 19.2% antiperspirant

PURPOSE

Reduces underarm perspiration

Keep out of reach of children. If swallowed, get medical help or contact a poison control center right away

Stop use if rash or irritation occurs

WARNINGS

For external use only. Do not use on broken skin. Ask a doctor before use if you have kidney disease.

DOSAGE AND ADMINISTRATION

apply to underarms only.

INACTIVE INGREDIENT

Arachidyl Alcohol, Carapa Guaianensis Seed oil, Dimethicone, Hydrogenated Castor oil, Fragrance (parfum), Phenyl Trimethicone, PPG-14 Butyl Ether, Stearyl Alcohol, Talc, Trisiloxane.

PACKAGE LABEL

Re-Charge Black pepper

anti-perspirant stick

Net WT. 2.6 oz. 75g